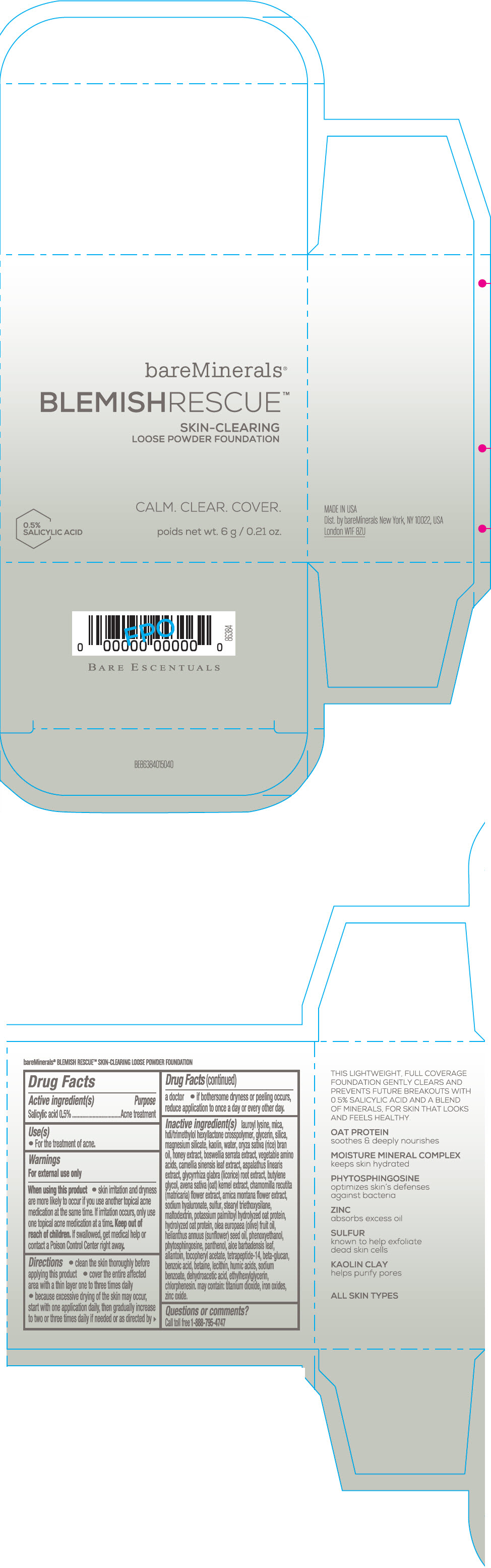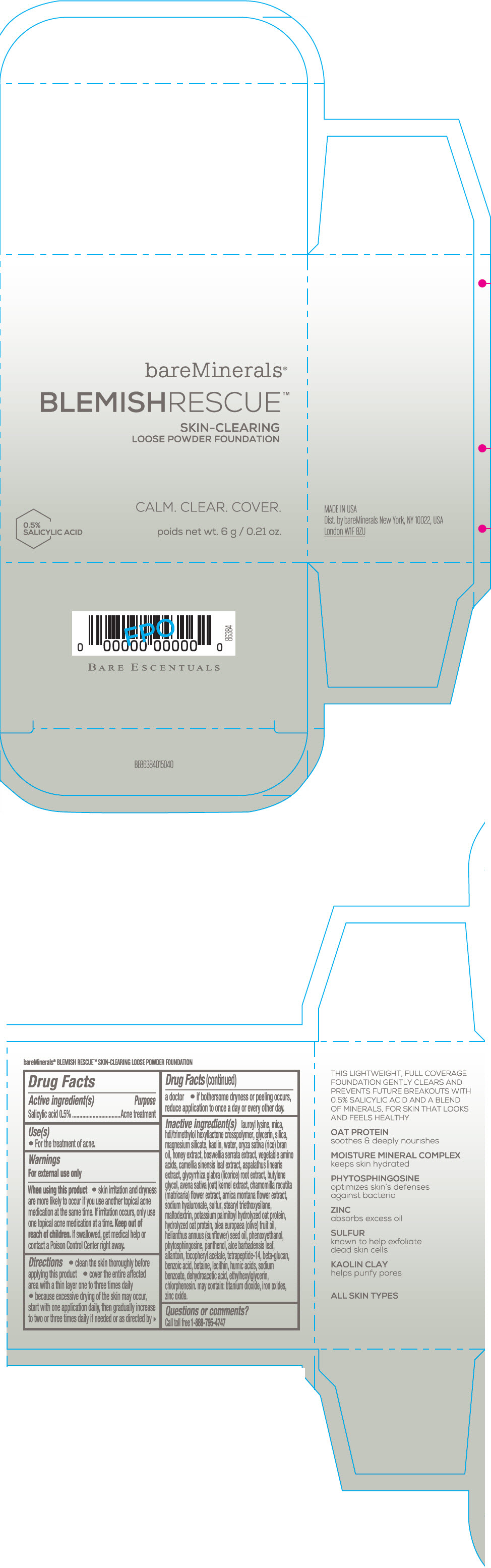 DRUG LABEL: bareMinerals Blemish Rescue Skin-Clearing Loose Foundation
NDC: 98132-231 | Form: POWDER
Manufacturer: Orveon Global US LLC
Category: otc | Type: HUMAN OTC DRUG LABEL
Date: 20241022

ACTIVE INGREDIENTS: SALICYLIC ACID 30 mg/6 g
INACTIVE INGREDIENTS: PHENOXYETHANOL; PHYTOSPHINGOSINE; PANTHENOL; ALOE VERA LEAF; ALLANTOIN; .ALPHA.-TOCOPHEROL ACETATE, DL-; BENZOIC ACID; BETAINE; LECITHIN, SOYBEAN; SODIUM BENZOATE; DEHYDROACETIC ACID; ETHYLHEXYLGLYCERIN; CHLORPHENESIN; TITANIUM DIOXIDE; FERRIC OXIDE RED; FERRIC OXIDE YELLOW; FERROSOFERRIC OXIDE; ZINC OXIDE; HEXAMETHYLENE DIISOCYANATE/TRIMETHYLOL HEXYLLACTONE CROSSPOLYMER; MICA; GLYCERIN; SILICON DIOXIDE; LAUROYL LYSINE; MAGNESIUM SILICATE; KAOLIN; WATER; RICE BRAN OIL; HONEY; INDIAN FRANKINCENSE; GREEN TEA LEAF; GLYCYRRHIZA GLABRA; BUTYLENE GLYCOL; OAT; CHAMOMILE; ARNICA MONTANA FLOWER; HYALURONATE SODIUM; SULFUR; STEARYL TRIETHOXYSILANE; MALTODEXTRIN; OLIVE OIL; SUNFLOWER OIL

bareMinerals® Blemish Rescue™ Skin-Clearing Loose Powder Foundation

Drug Facts

Active ingredients

Salicylic acid 0.5%

Purpose

Acne treatment

Uses

- For the treatment of acne.

Warning

For external use only

When using this product

- skin irritation and dryness is more likely to occur if you use another topical acne medication at the same time. If irritation occurs, only use one topical acne medication at a time.

- keep out of reach of children
- if swallowed, get medical help or contact a Poison Control Center right away

Directions

- clean the skin thoroughly before applying this product
- cover the entire affected area with a thin layer one to three times daily
- because excessive drying of the skin may occur, start with one application daily, then gradually increase to two or three times daily if needed or as directed by a doctor
- if bother some dryness or peeling occurs, reduce application to once a day or every other day."

Inactive Ingredients

lauroyl lysine, hdi/trimethylol hexyllactone crosspolymer, mica, glycerin, silica, magnesium silicate, kaolin, water, oryza sativa (rice) bran oil, honey extract, boswellia serrata extract, vegetable amino acids, camellia sinensis leaf extract, aspalathus linearis extract, glycyrrhiza glabra (licorice) root extract, butylene glycol, avena sativa (oat) kernel extract, chamomilla recutita (matricaria) flower extract, arnica montana flower extract, sodium hyaluronate, sulfur, stearyl triethoxysilane, maltodextrin, potassium palmitoyl hydrolyzed oat protein, hydrolyzed oat protein, olea europaea (olive) fruit oil, helianthus annuus (sunflower) seed oil, phenoxyethanol, phytosphingosine, panthenol, aloe barbadensis leaf, allantoin, tocopheryl acetate, tetrapeptide-14, beta-glucan, benzoic acid, betaine, lecithin, humic acids, sodium benzoate, dehydroacetic acid, ethylhexylglycerin, chlorphenesin. may contain: titanium dioxide, iron oxides, zinc oxide.

Questions or comments?

Call toll free 1-800-795-4747

Dist. by bareMinerals New York, NY 10022, USA

PRINCIPAL DISPLAY PANEL - 6 g Jar Carton - Fair 1C

bareMinerals®
BLEMISHRESCUE™
SKIN-CLEARING
LOOSE POWDER FOUNDATION

CALM. CLEAR. COVER.

0.5%
SALICYLIC ACID

net wt. 6 g / 0.21 oz.

PRINCIPAL DISPLAY PANEL - 6 g Jar Carton - Fair Ivory 1N

bareMinerals®
BLEMISHRESCUE™
SKIN-CLEARING
LOOSE POWDER FOUNDATION

CALM. CLEAR. COVER.

0.5%
SALICYLIC ACID

net wt. 6 g / 0.21 oz.

PRINCIPAL DISPLAY PANEL - 6 g Jar Carton - Fairly Light 1 NW

bareMinerals®
BLEMISHRESCUE™
SKIN-CLEARING
LOOSE POWDER FOUNDATION

CALM. CLEAR. COVER.

0.5%
SALICYLIC ACID

net wt. 6 g / 0.21 oz.

PRINCIPAL DISPLAY PANEL - 6 g Jar Carton - Fairly Medium 1.5C

bareMinerals®
BLEMISHRESCUE™
SKIN-CLEARING
LOOSE POWDER FOUNDATION

CALM. CLEAR. COVER.

0.5%
SALICYLIC ACID

net wt. 6 g / 0.21 oz.

PRINCIPAL DISPLAY PANEL - 6 g Jar Carton - Neutral Ivory 2N

bareMinerals®
BLEMISHRESCUE™
SKIN-CLEARING
LOOSE POWDER FOUNDATION

CALM. CLEAR. COVER.

0.5%
SALICYLIC ACID

net wt. 6 g / 0.21 oz.

PRINCIPAL DISPLAY PANEL - 6 g Jar Carton - Light 2W

bareMinerals®
BLEMISHRESCUE™
SKIN-CLEARING
LOOSE POWDER FOUNDATION

CALM. CLEAR. COVER.

0.5%
SALICYLIC ACID

net wt. 6 g / 0.21 oz.

PRINCIPAL DISPLAY PANEL - 6 g Jar Carton - Medium 3C

bareMinerals®
BLEMISHRESCUE™
SKIN-CLEARING
LOOSE POWDER FOUNDATION

CALM. CLEAR. COVER.

0.5%
SALICYLIC ACID

net wt. 6 g / 0.21 oz.

PRINCIPAL DISPLAY PANEL - 6 g Jar Carton - Soft Medium 2CN

bareMinerals®
BLEMISHRESCUE™
SKIN-CLEARING
LOOSE POWDER FOUNDATION

CALM. CLEAR. COVER.

0.5%
SALICYLIC ACID

net wt. 6 g / 0.21 oz.

PRINCIPAL DISPLAY PANEL - 6 g Jar Carton - Medium Beige 2.5N

bareMinerals®
BLEMISHRESCUE™
SKIN-CLEARING
LOOSE POWDER FOUNDATION

CALM. CLEAR. COVER.

0.5%
SALICYLIC ACID

net wt. 6 g / 0.21 oz.

PRINCIPAL DISPLAY PANEL - 6 g Jar Carton - Golden Beige 2.5NW

bareMinerals®
BLEMISHRESCUE™
SKIN-CLEARING
LOOSE POWDER FOUNDATION

CALM. CLEAR. COVER.

0.5%
SALICYLIC ACID

net wt. 6 g / 0.21 oz.

PRINCIPAL DISPLAY PANEL - 6 g Jar Carton - Neutral Medium 3N

bareMinerals®
BLEMISHRESCUE™
SKIN-CLEARING
LOOSE POWDER FOUNDATION

CALM. CLEAR. COVER.

0.5%
SALICYLIC ACID

net wt. 6 g / 0.21 oz.

PRINCIPAL DISPLAY PANEL - 6 g Jar Carton - Golden Nude 3.5NW

bareMinerals®
BLEMISHRESCUE™
SKIN-CLEARING
LOOSE POWDER FOUNDATION

CALM. CLEAR. COVER.

0.5%
SALICYLIC ACID

net wt. 6 g / 0.21 oz.

PRINCIPAL DISPLAY PANEL - 6 g Jar Carton - Tan Nude 3.5W

bareMinerals®
BLEMISHRESCUE™
SKIN-CLEARING
LOOSE POWDER FOUNDATION

CALM. CLEAR. COVER.

0.5%
SALICYLIC ACID

net wt. 6 g / 0.21 oz.

PRINCIPAL DISPLAY PANEL - 6 g Jar Carton - Medium Tan 3.5CN

bareMinerals®
BLEMISHRESCUE™
SKIN-CLEARING
LOOSE POWDER FOUNDATION

CALM. CLEAR. COVER.

0.5%
SALICYLIC ACID

net wt. 6 g / 0.21 oz.

PRINCIPAL DISPLAY PANEL - 6 g Jar Carton - Neutral Tan 4N

bareMinerals®
BLEMISHRESCUE™
SKIN-CLEARING
LOOSE POWDER FOUNDATION

CALM. CLEAR. COVER.

0.5%
SALICYLIC ACID

net wt. 6 g / 0.21 oz.

PRINCIPAL DISPLAY PANEL - 6 g Jar Carton - Warm Tan 4.5CN

bareMinerals®
BLEMISHRESCUE™
SKIN-CLEARING
LOOSE POWDER FOUNDATION

CALM. CLEAR. COVER.

0.5%
SALICYLIC ACID

net wt. 6 g / 0.21 oz.

PRINCIPAL DISPLAY PANEL - 6 g Jar Carton - Medium Dark 5CN

bareMinerals®
BLEMISHRESCUE™
SKIN-CLEARING
LOOSE POWDER FOUNDATION

CALM. CLEAR. COVER.

0.5%
SALICYLIC ACID

net wt. 6 g / 0.21 oz.

PRINCIPAL DISPLAY PANEL - 6 g Jar Carton - Warm Deep 5.5N

bareMinerals®
BLEMISHRESCUE™
SKIN-CLEARING
LOOSE POWDER FOUNDATION

CALM. CLEAR. COVER.

0.5%
SALICYLIC ACID

net wt. 6 g / 0.21 oz.

PRINCIPAL DISPLAY PANEL - 6 g Jar Carton - Neutral Deep 5.5NW

bareMinerals®
BLEMISHRESCUE™
SKIN-CLEARING
LOOSE POWDER FOUNDATION

CALM. CLEAR. COVER.

0.5%
SALICYLIC ACID

net wt. 6 g / 0.21 oz.

PRINCIPAL DISPLAY PANEL - 6 g Jar Carton - Deepest Deep 6C

bareMinerals®
BLEMISHRESCUE™
SKIN-CLEARING
LOOSE POWDER FOUNDATION

CALM. CLEAR. COVER.

0.5%
SALICYLIC ACID

net wt. 6 g / 0.21 oz.